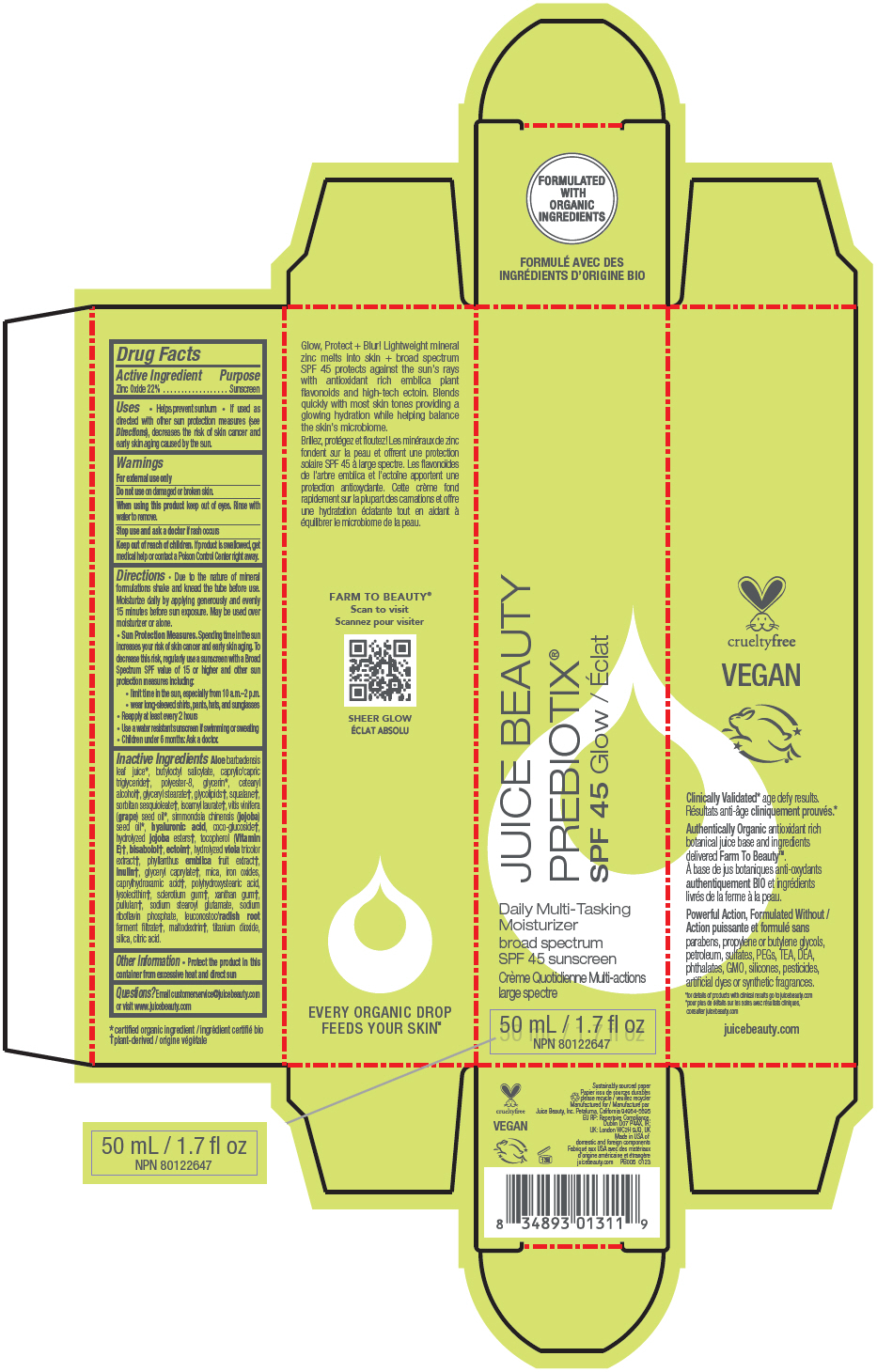 DRUG LABEL: PREBIOTIX SPF 45 Glow
NDC: 55165-0301 | Form: LOTION
Manufacturer: Juice Beauty
Category: otc | Type: HUMAN OTC DRUG LABEL
Date: 20241224

ACTIVE INGREDIENTS: Zinc Oxide 22 g/100 mL
INACTIVE INGREDIENTS: ALOE VERA LEAF; BUTYLOCTYL SALICYLATE; MEDIUM-CHAIN TRIGLYCERIDES; POLYESTER-8 (1400 MW, CYANODIPHENYLPROPENOYL CAPPED); GLYCERIN; CETOSTEARYL ALCOHOL; GLYCERYL STEARATE SE; PSEUDOMONAS GLUCOSE FERMENTATION RHAMNOLIPIDS; SQUALANE; SORBITAN SESQUIOLEATE; ISOAMYL LAURATE; GRAPE SEED OIL; JOJOBA OIL; HYALURONIC ACID; COCO-GLUCOSIDE; POTASSIUM HYDROLYZED JOJOBA ESTERS; TOCOPHEROL; LEVOMENOL; ECTOINE; VIOLA TRICOLOR WHOLE; PHYLLANTHUS EMBLICA FRUIT; INULIN; GLYCERYL MONOCAPRYLATE; MICA; FERRIC OXIDE YELLOW; CAPRYLHYDROXAMIC ACID; POLYHYDROXYSTEARIC ACID (2300 MW); LYSOPHOSPHATIDYLCHOLINE, SOYBEAN; BETASIZOFIRAN; XANTHAN GUM; PULLULAN; SODIUM STEAROYL GLUTAMATE; RIBOFLAVIN 5'-PHOSPHATE SODIUM ANHYDROUS; LEUCONOSTOC/RADISH ROOT FERMENT FILTRATE; MALTODEXTRIN; TITANIUM DIOXIDE; SILICON DIOXIDE; CITRIC ACID MONOHYDRATE

PREBIOTIX® SPF 45 Glow

Drug Facts

Active Ingredient

Zinc Oxide 22%

Purpose

Sunscreen

Uses

- Helps prevent sunburn
- If used as directed with other sun protection measures (see Directions), decreases the risk of skin cancer and early skin aging caused by the sun.

Warnings

For external use only

Do not use on damaged or broken skin.

When using this product keep out of eyes. Rinse with water to remove.

Stop use and ask a doctor if rash occurs

Keep out of reach of children. If product is swallowed, get medical help or contact a Poison Control Center right away.

Directions

- Due to the nature of mineral formulations shake and knead the tube before use. Moisturize daily by applying generously and evenly 15 minutes before sun exposure. May be used over moisturizer or alone.
- Sun Protection Measures. Spending time in the sun increases your risk of skin cancer and early skin aging. To decrease this risk, regularly use a sunscreen with a Broad Spectrum SPF value of 15 or higher and other sun protection measures including:
  - limit time in the sun, especially from 10 a.m.–2 p.m.
  - wear long-sleeved shirts, pants, hats, and sunglasses
- Reapply at least every 2 hours
- Use a water resistant sunscreen if swimming or sweating
- Children under 6 months: Ask a doctor.

Inactive Ingredients

Aloe barbadensis leaf juice [certified organic ingredient] , butyloctyl salicylate, caprylic/capric triglyceride [plant-derived] , polyester-8, glycerin, cetearyl alcohol, glyceryl stearate, glycolipids, squalane, sorbitan sesquioleate, isoamyl laurate, vitis vinifera (grape) seed oil, simmondsia chinensis (jojoba) seed oil, hyaluronic acid, coco-glucoside, hydrolyzed jojoba esters, tocopherol (Vitamin E), bisabolol, ectoin, hydrolyzed viola tricolor extract, phyllanthus emblica fruit extract, inulin, glyceryl caprylate, mica, iron oxides, caprylhydroxamic acid, polyhydroxystearic acid, lysolecithin, sclerotium gum, xanthan gum, pullulan, sodium stearoyl glutamate, sodium riboflavin phosphate, leuconostoc/radish root ferment filtrate, maltodextrin, titanium dioxide, silica, citric acid.

Other Information

- Protect the product in this container from excessive heat and direct sun

Questions?

Email customerservice@juicebeauty.com or visit www.juicebeauty.com

PRINCIPAL DISPLAY PANEL - 50 mL Tube Carton

JUICE BEAUTY
PREBIOTIX®
SPF 45 Glow

Daily Multi-Tasking
Moisturizer

broad spectrum
SPF 45 sunscreen

50 mL / 1.7 fl oz
NPN 80122647